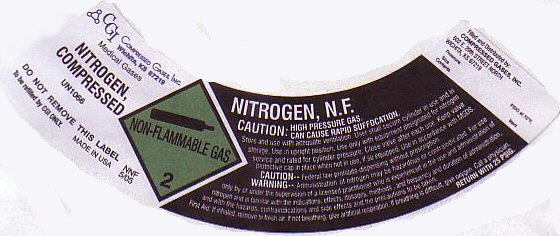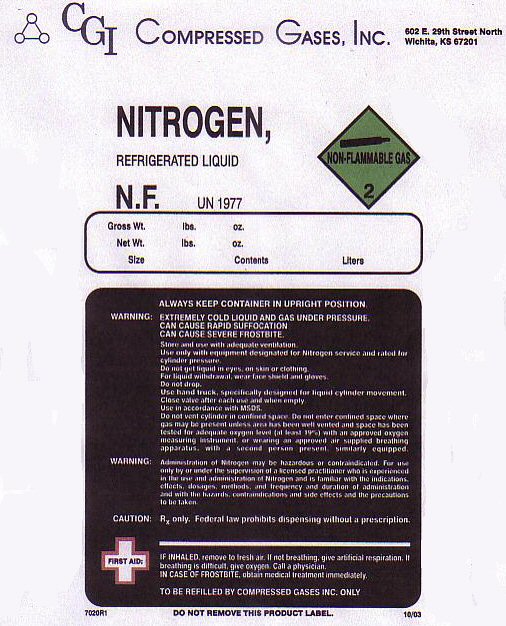 DRUG LABEL: NITROGEN
NDC: 34330-002 | Form: GAS
Manufacturer: Compressed Gases Inc
Category: prescription | Type: HUMAN PRESCRIPTION DRUG LABEL
Date: 20100101

ACTIVE INGREDIENTS: NITROGEN 99 L/100 L

NITROGEN NF COMPRESSED LABEL

NITROGEN COMPRESSED NITROGEN N.F. NON-FLAMMABLE GAS-2 UN 1066

USE IN UPRIGHT POSITION. USE ONLY WITH EQUIPMENT DESIGNATED FOR NITROGEN SERVICE AND RATED FOR CYLINDER PRESSURE. CLOSE VALVE AFTER EACH USE. KEEP VALVE PROTECTIVE CAP IN PLACE WHEN NOT IN USE IF SO EQUIPPED. USE IN ACCORDANCE WITH MSDS. RETURN WITH 25 PSIG DO NOT REMOVE THIS PRODUCT LABEL

NNF 5/05

PRESSURE__________ PSIG AT 70 F SIZE _________ CONTENTS________LITERS

NITROGEN NF REFRIGERATED LIQUID

NITROGEN REFRIGERATED LIQUID N.F. UN 1977 NON-FLAMMABLE GAS-2

GROSS WT_____LBS ______OZ

NET WT ____LBS ____OZ

SIZE_____ CONTENTS______________LITERS

ALWAYS KEEP CONTAINER IN UPRIGHT POSITION.

WARNING: EXTREMELY COLD LIQUID AND GAS UNDER PRESSURE CAN CAUSE RAPID SUFFOCATION CAN CAUSE SEVERE FROSTBITE.

USE ONLY WITH EQUIPMENT DESIGNATED FOR NITROGEN SERVICE AND RATED FOR CYLINDER PRESSURE. DO NOT GET LIQUID IN EYES, ON SKIN OR CLOTHING. FOR LIQUID WITHDRAWAL WEAR FACE SHIELD AND GLOVES. DO NOT DROP. USE HAND TRUCK SPECIFICALLY DESIGNED FOR LIQUID CYLINDER MOVEMENT. CLOSE VALVE AFTER EACH USE AND WHEN EMPTY. USE IN ACCORDANCE WITH MSDS.

DO NOT VENT CYLINDER IN CONFINED SPACE. DO NOT ENTER CONFINED SPACE WHERE GAS MAY BE PRESENT UNLESS AREA HAS BEEN WELL VENTED AND SPACE HAS BEEN TESTED FOR ADEQUATE OXYGEN LEVEL (AT LEAST 19%) WITH AN APPROVED OXYGEN MEASURING INSTRUMENT OR WEARING AN APPROVED AIR SUPPLIED BREATHING APPARATUS WITH A SECOND PERSON PRESENT SIMILARLY EQUIPPED.

Rx ONLY. FEDERAL LAW PROHIBITS DISPENSING WITHOUT A PRESCRIPTION.

7020R1 10/03 DO NOT REMOVE THIS PRODUCT LABEL

PRODUCT WARNINGS AND PRECAUTIONS

CAUTION: HIGH PRESSURE GAS. CAN CAUSE RAPID SUFFOCATION. STORE AND USE WITH ADEQUATE VENTILATION. USER SHALL SECURE CYLINDER IN USE AND IN STORAGE.

CAUTION: FEDERAL LAW PROHIBITS DISPENSING OF NITROGEN WITHOUT A PRESCRIPTION

WARNING: ADMINISTRATION OF NITROGEN MAY BE HAZARDOUS OR CONTRAINDICATED. FOR USE ONLY BY OUR UNDER THE SUPERVISION OF A LICENSED PRACTITIONER WHO IS EXPERIENCED IN THE USE AND ADMINISTRATION OF NITROGEN AND IS FAMILIAR WITH THE INDICATIONS, EFFECTS, DOSAGES, METHODS, AND FREQUENCY AND DURATION OF ADMINISTRATION AND WITH THE HAZARDS, CONTRAINDICATIONS AND SIDE EFFECTS AND THE PRECAUTIONS TO BE TAKEN.

FIRST AID: IF INHALED REMOVE TO FRESH AIR. IF NOT BREATHING GIVE ARTIFICIAL RESPIRATION. IF BREATHING IS DIFFICULT GIVE OXYGEN. CALL A PHYSICIAN.